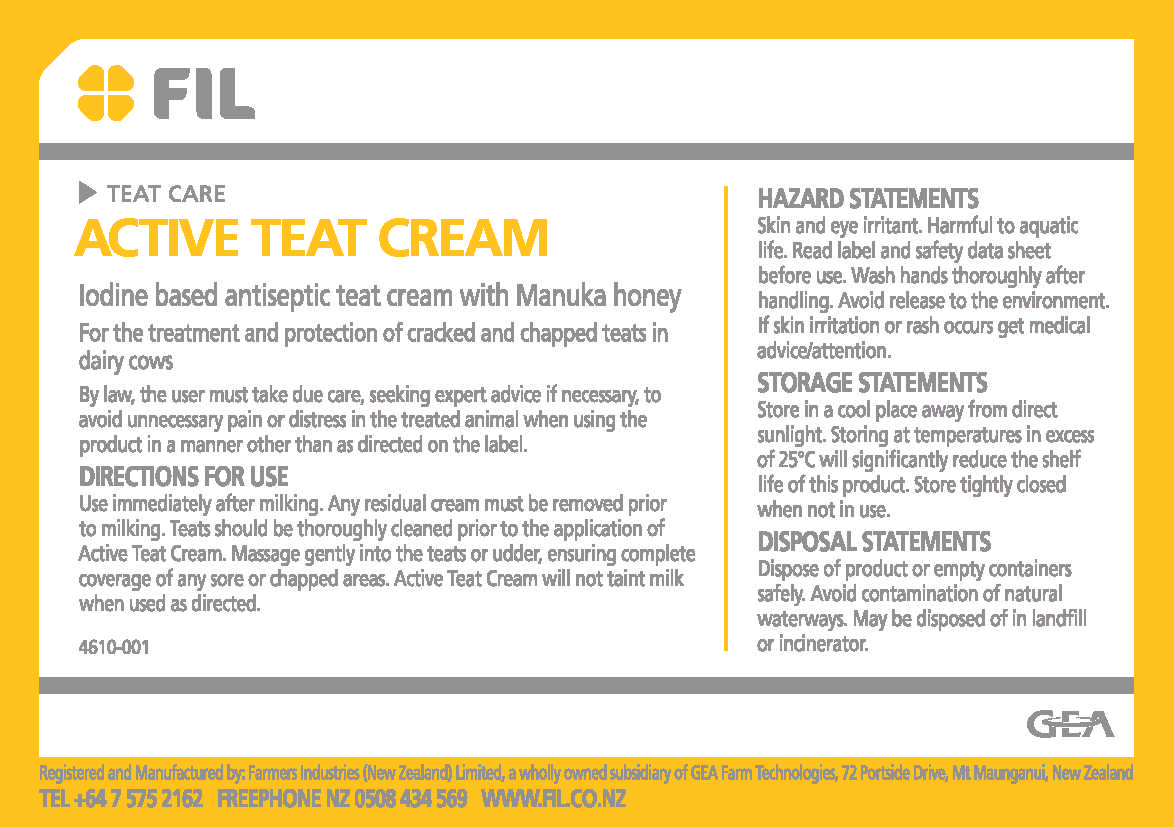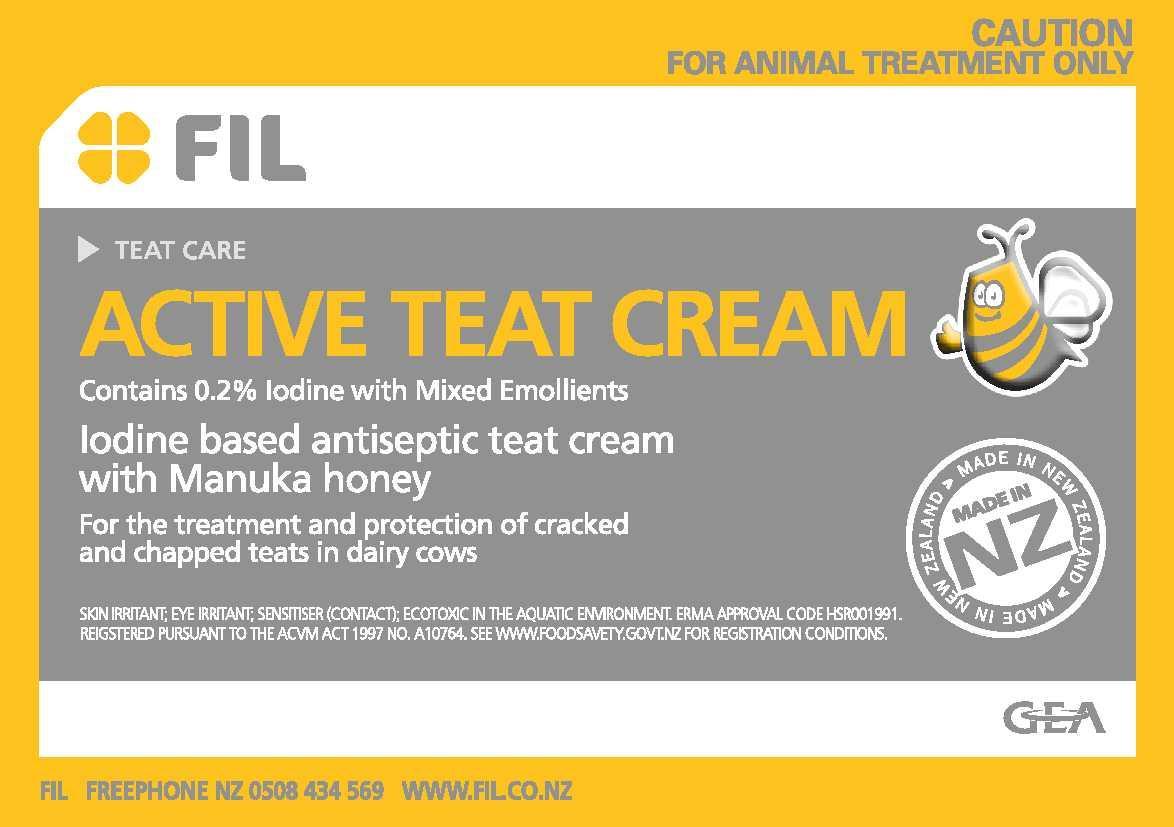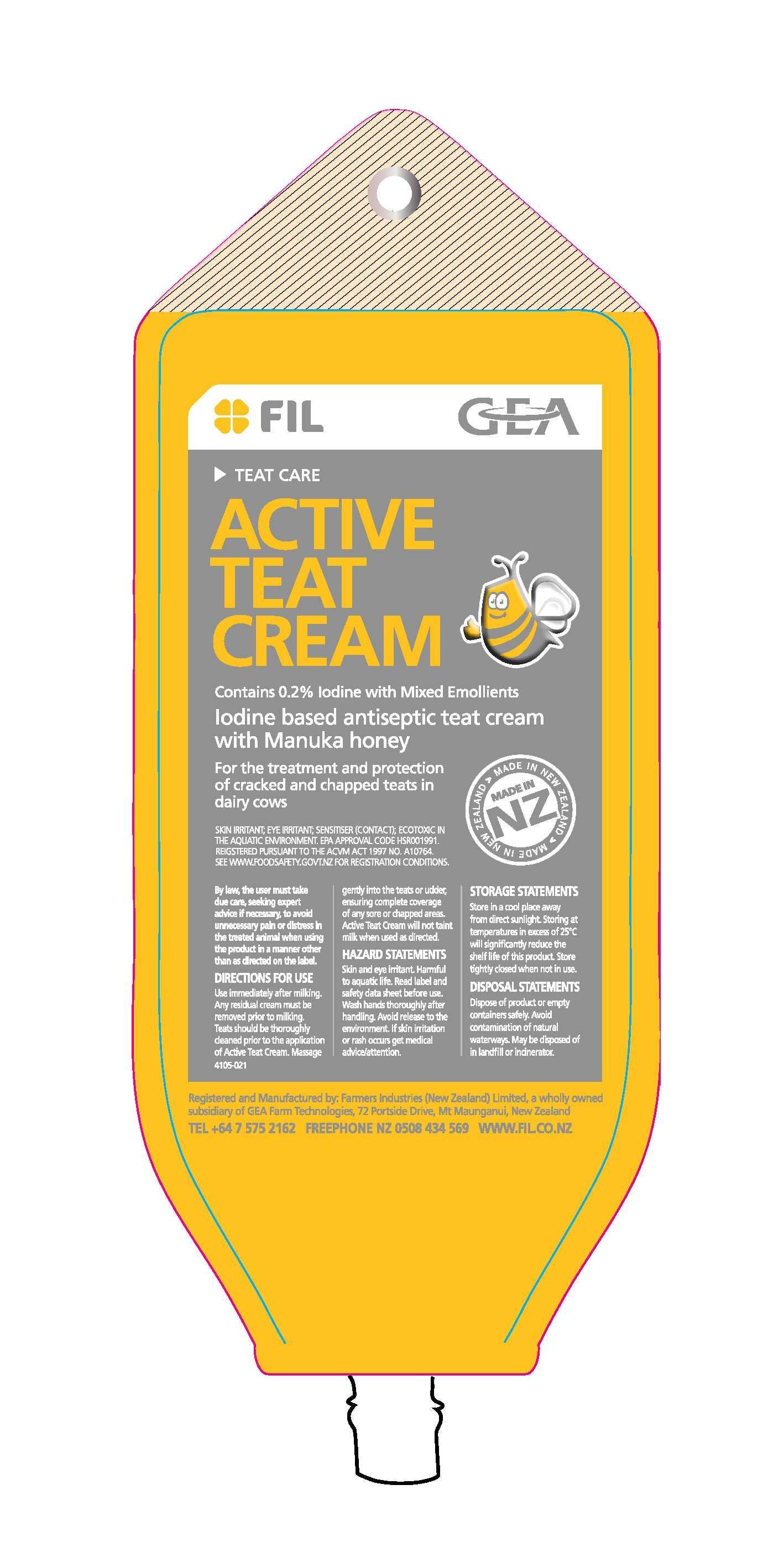 DRUG LABEL: Active Teat Cream
NDC: 51546-002 | Form: CREAM
Manufacturer: Farmers Industries (New Zealand) Limited
Category: animal | Type: OTC ANIMAL DRUG LABEL
Date: 20220722

ACTIVE INGREDIENTS: IODINE 100 g/100 g

ACTIVE TEAT CREAM

SAFE HANDLING WARNING

CAUTION

FOR ANIMAL TREATMENT ONLY

TEAT CARE

ACTIVE INGREDIENT

Contains 0.2% Iodine with Mixed Emollients

INDICATIONS AND USAGE

For the treatment and protection of cracked and chapped teats in dairy cows

SKIN IRRITANT; EYE IRRITANT; SENSITISER (CONTACT); ECOTOXIC IN THE AQUATIC ENVIRONMENT. ERMA APPROVAL CODE HSR001991. REGISTERED PURSUANT TO THE ACVM ACT 1997 NO. A10764. SE WWW.FOODSAFETY.GOV.NZ FOR REGISTRATION CONDITIONS.

MADE IN NEW ZEALAND

By law, the user must take due care, seeking expert advice if necessary, to avoid unnecessary pain or distress in the treated animal when using the product in a manner other than as directed on the label.

DOSAGE AND ADMINISTRATION

DIRECTIONS FOR USE

Use immediately after milking. Any residual cream must be removed prior to milking. Teats should be thoroughly cleaned prior to the application of Active teat Cream. Massage gently into the teats or udder, ensuring complete coverage of any sore or chapped areas. Active Teat Cream will not taint milk when used as directed.

PRECAUTIONS

HAZARD STATEMENTS

Skin and eye irritant. Harmful to aquatic life. Read label and safety data sheet before use. Wash hands thoroughly after handling. Avoid release to the environment. If skin irritation or rash occurs get medical advice/attention.

STORAGE STATEMENTS

Store in a cool place away from direct sunlight. Storing at temperatures in excess of 25°C will significantly reduce the shelf life of this product. Store tightly closed when not in use.

DISPOSAL STATEMENTS

Dispose of product or empty containers safely. Avoid contamination of natural waterways. May be disposed of in landfill or incinerator.

GEA

FIL

4610-001

4105-021

Registered and Manufactured by: Farmers Industries (New Zealand) Limited, a wholly owned subsidiary of GEA Farm Technologies, 72 Portside Drive, Mt. Maunganui, New Zealand

TEL +64 7 575 2162 FREEPHONE NZ 0508 434 569 WWW.FIL.CO.NZ

PACKAGE LABEL

ACTIVE TEAT CREAM

Iodine based antiseptic teat cream with Manuka honey